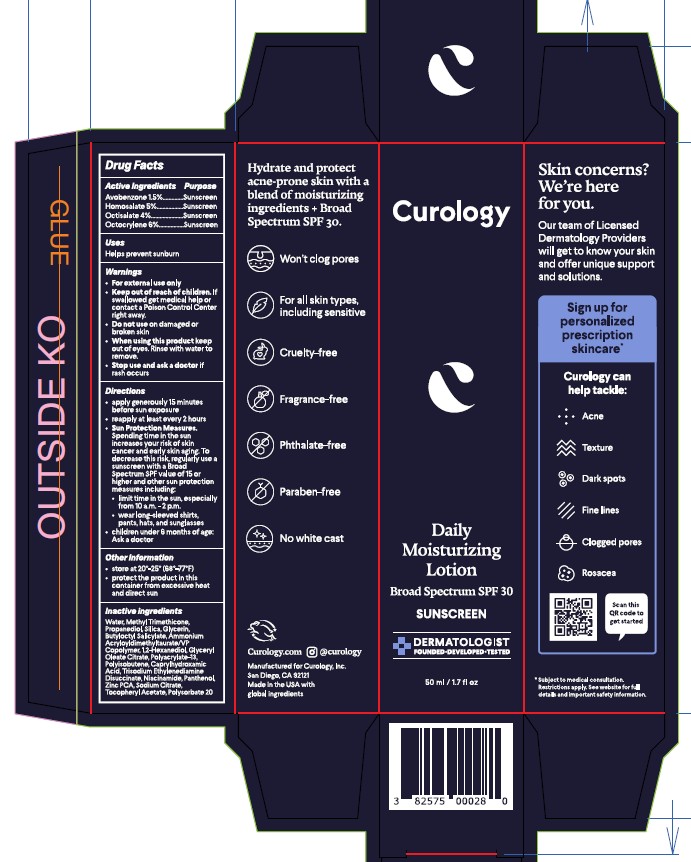 DRUG LABEL: Curology Daily Moisturizing
NDC: 82575-400 | Form: CREAM
Manufacturer: Curology, Inc
Category: otc | Type: HUMAN OTC DRUG LABEL
Date: 20250811

ACTIVE INGREDIENTS: OCTISALATE 4 g/100 mL; HOMOSALATE 5 g/100 mL; OCTOCRYLENE 6 g/100 mL; AVOBENZONE 1.5 g/100 mL
INACTIVE INGREDIENTS: ZINC PCA; WATER; PROPANEDIOL; SODIUM CITRATE; BUTYLOCTYL SALICYLATE; 1,2-HEXANEDIOL; METHYL TRIMETHICONE; AMMONIUM ACRYLOYLDIMETHYLTAURATE/VP COPOLYMER; POLYSORBATE 20; POLYACRYLATE-13; SILICON DIOXIDE; GLYCERYL OLEATE CITRATE; PANTHENOL; .ALPHA.-TOCOPHEROL ACETATE, DL-; GLYCERIN; CAPRYLHYDROXAMIC ACID; TRISODIUM ETHYLENEDIAMINE DISUCCINATE; NIACINAMIDE; HYDROGENATED POLYISOBUTENE (1300 MW)

Curology Daily Moisturizing Lotion Broad Spectrum SPF 30

Drug Facts

Active Ingredients

Active Ingredients | Purpose
Avobenzone 1.5% | Sunscreen
Homosalate 5% | Sunscreen
Octisalate 4% | Sunscreen
Octocrylene 6% | Sunscreen

Uses

Helps prevent sunburn

WARNINGS

- For external use only

- Keep out of reach of children. If swallowed get medical help or contact a Poinson Control Center right away.

- Do not use on damaged or broken skin

- When using this product keep out of eyes. Rinse with water to remove.

- Stop use and ask a doctor if rash occurs

Directions

- Apply generously 15 minutes before sun exposrue
- Reapply at least every 2 hours
- Sun Protection Measures. Spending time in the sun increases your risk of skin cancer and early skin aging. To decrease this risk, regularly use a sunscreen with a Broad Spectrum SPF value of 15 or higher and other sun protection measures including: - Limit time in the sun, especially from 10 a.m. - 2 p.m. - Wear long-sleeved shirts, pants, hats, and sunglasses
- Children under 6 months of age: Ask a doctor

Other Information

- Store at 20o - 25o (68o-77oF)
- Protect the product in this container from excessive heat and direct sun

Inactive Ingredients

Water, Methyl Trimethicone, Propanediol, Silica, Glycerin, Butyloctyl Salicylate, Ammonium Acryloyldimethyltaurate/VP Copolymer, 1,2-Hexanediol, Glyceryl Oleate Citrate, Polyacrylate-13, Polyisobutene, Caprylhydroxamic Acid, Trisodium Ethylenediamine Dissuccinate, Niacinamide, Panthenol, Zinc PCA, Sodium Citrate, Tocopheryl Acetate, Polysorbate 20

PRINCIPAL DISPLAY PANEL - 50 mL Tube Carton

Curology

Daily

Moisturizing

Lotion

Broad Spectrum SPF 30

SUNSCREEN

Dermatologist Founded, Developed, Tested

50 ml / 1.7 fl oz